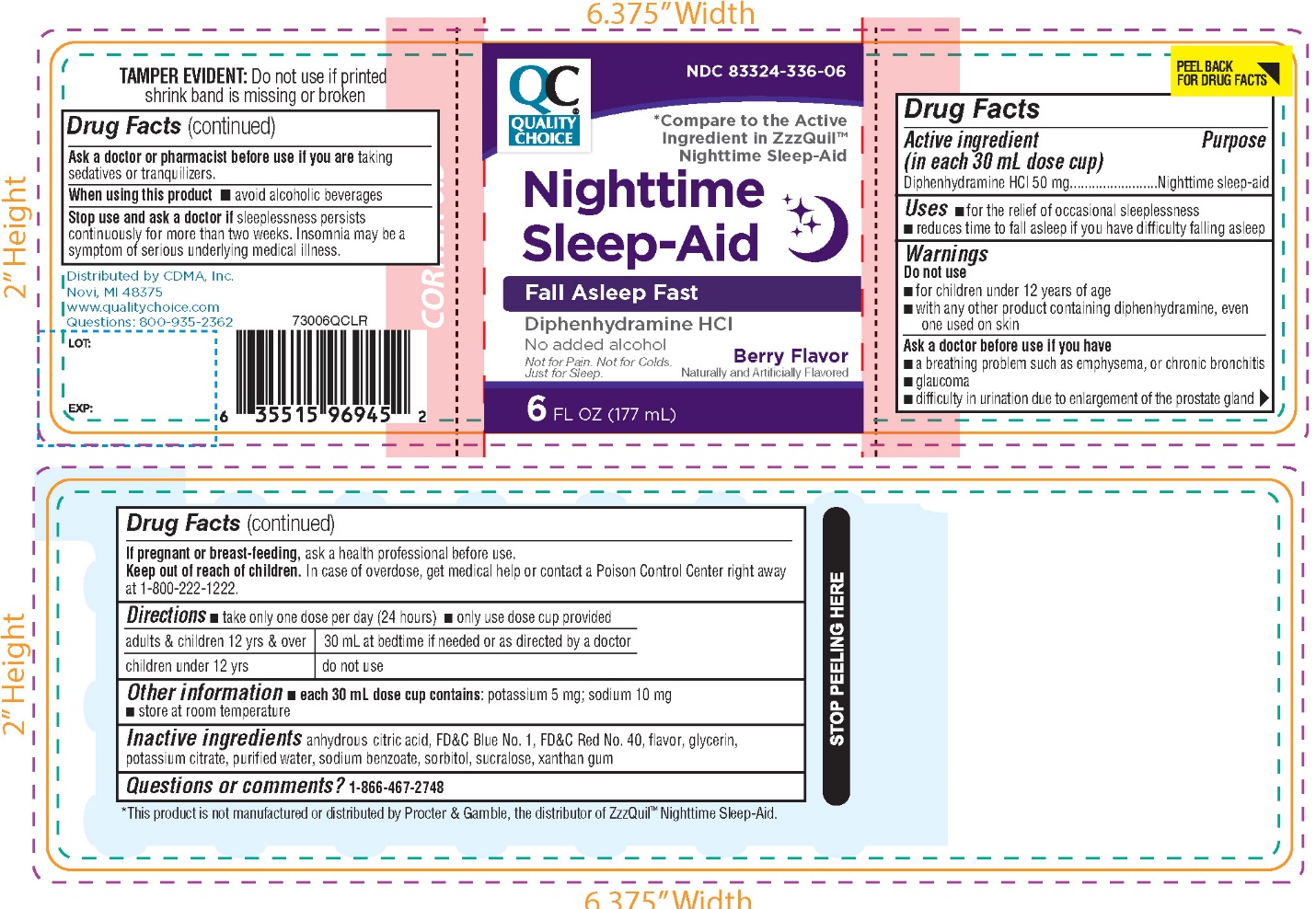 DRUG LABEL: QUALITY CHOICE

NDC: 83324-336 | Form: LIQUID
Manufacturer: QUALITY CHOICE (CHAIN DRUG MARKETING ASSOCIATION)
Category: otc | Type: HUMAN OTC DRUG LABEL
Date: 20250823

ACTIVE INGREDIENTS: DIPHENHYDRAMINE HYDROCHLORIDE 50 mg/30 mL
INACTIVE INGREDIENTS: ANHYDROUS CITRIC ACID; FD&C BLUE NO. 1; FD&C RED NO. 40; GLYCERIN; POTASSIUM CITRATE; WATER; SODIUM BENZOATE; SORBITOL; SUCRALOSE; XANTHAN GUM

Quality Choice Nighttime Sleep-Aid

Drug Facts

Active ingredient (in each 30 mL dose cup)

Diphenhydramine HCl 50 mg

Purpose

Nighttime sleep-aid

Uses

- for the relief of occasional sleeplessness
- reduces time to fall asleep if you have difficulty falling asleep

Warnings

Do not use

- for children under 12 years of age
- with any other product containing diphenhydramine, even one used on skin

Ask a doctor before use if you have

- a breathing problem such as emphysema, or chronic bronchitis
- glaucoma
- difficulty in urination due to enlargement of the prostate gland

Ask a doctor or pharmacist before use if you aretaking sedatives or tranquilizers.

When using this product

- avoid alcoholic beverages.

Stop use and ask a doctor ifsleeplessness persists continuously for more than two weeks. Insomnia may be a symptom of serious underlying medical illness.

PREGNANCY OR BREAST FEEDING

If pregnant or breast-feeding, ask a health professional before use.

Keep out of reach of children.

In case of overdose, get medical help or contact a Poison Control Center right away at 1-800-222-1222.

Directions

- take only one dose per day (24 hours)
- Only use dose cup provided.

adults & children 12 yrs & over | 30 mL at bedtime if needed or as directed by a doctor
children under 12 yrs | do not use

Other information

- each 30 mL dose contains: potassium 5 mg; sodium 10 mg
- store at room temperature

Inactive ingredients

anhydrous citric acid, FD&C blue 1, FD&C red 40, flavor, glycerin, potassium citrate, purified water, sodium benzoate, sorbitol, sucralose, xanthan gum.

Questions or comments?

1-866-467-2748

PRINCIPAL DISPLAY PANEL

QUALITY CHOICE

NDC 83324-336-06

*Compare to the active ingredient in ZzzQuil™Nighttime Sleep-Aid

Nighttime Sleep-Aid

Fall Asleep Fast

Diphenhydramine HCl

No added alcohol

Not for Pain. Not for Colds.

Just for sleep.

Berry Flavor

Naturally & Artificially Flavored

6 FL OZ (177 mL)

TAMPER EVIDENT: Do not use if printed shrink band is missing or broken

DISTRIBUTED BY: CDMA, Inc,

Novi, MI 48375

www.qualitychoice.com

Questions: 800-935-2362

*This product is not manufactured or distributed by Procter & Gamble, the distributor of ZzzQuil™ Nighttime Sleep-Aid.